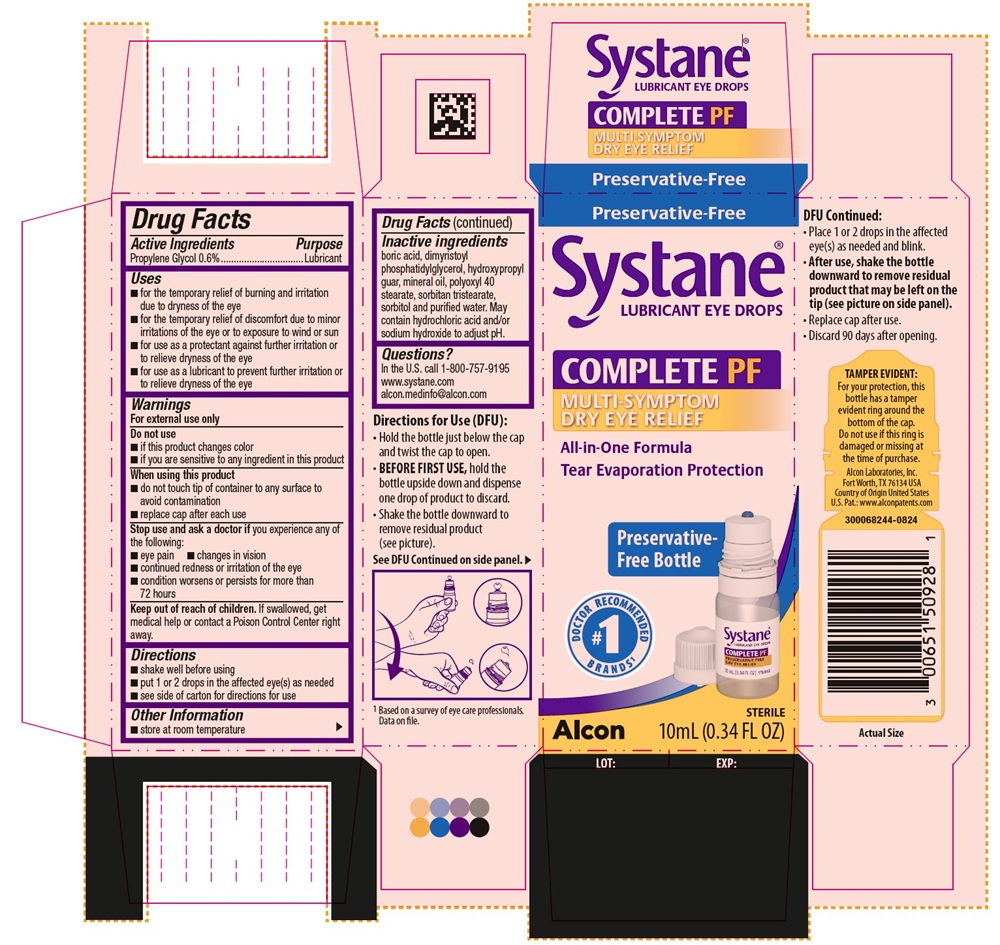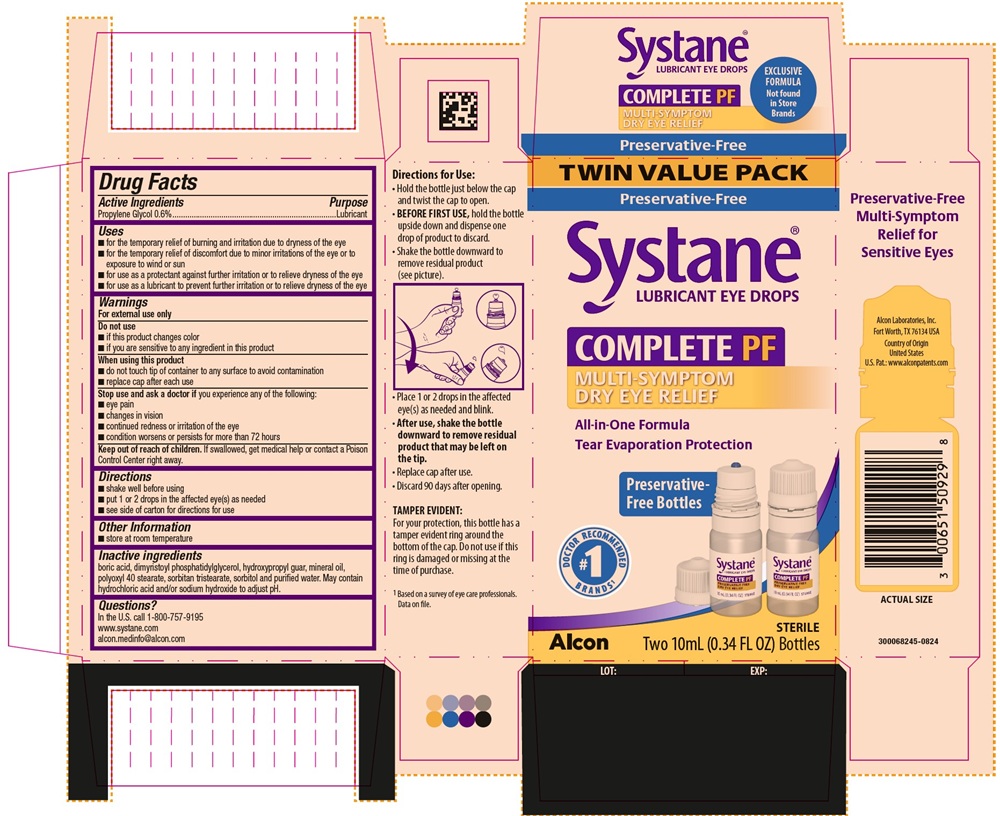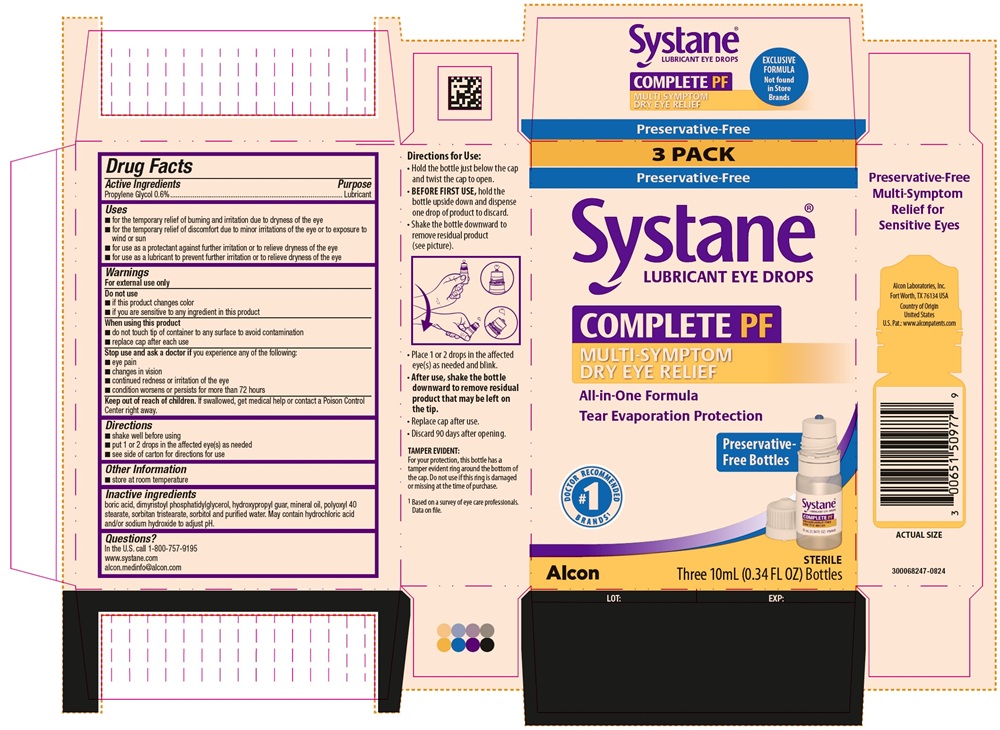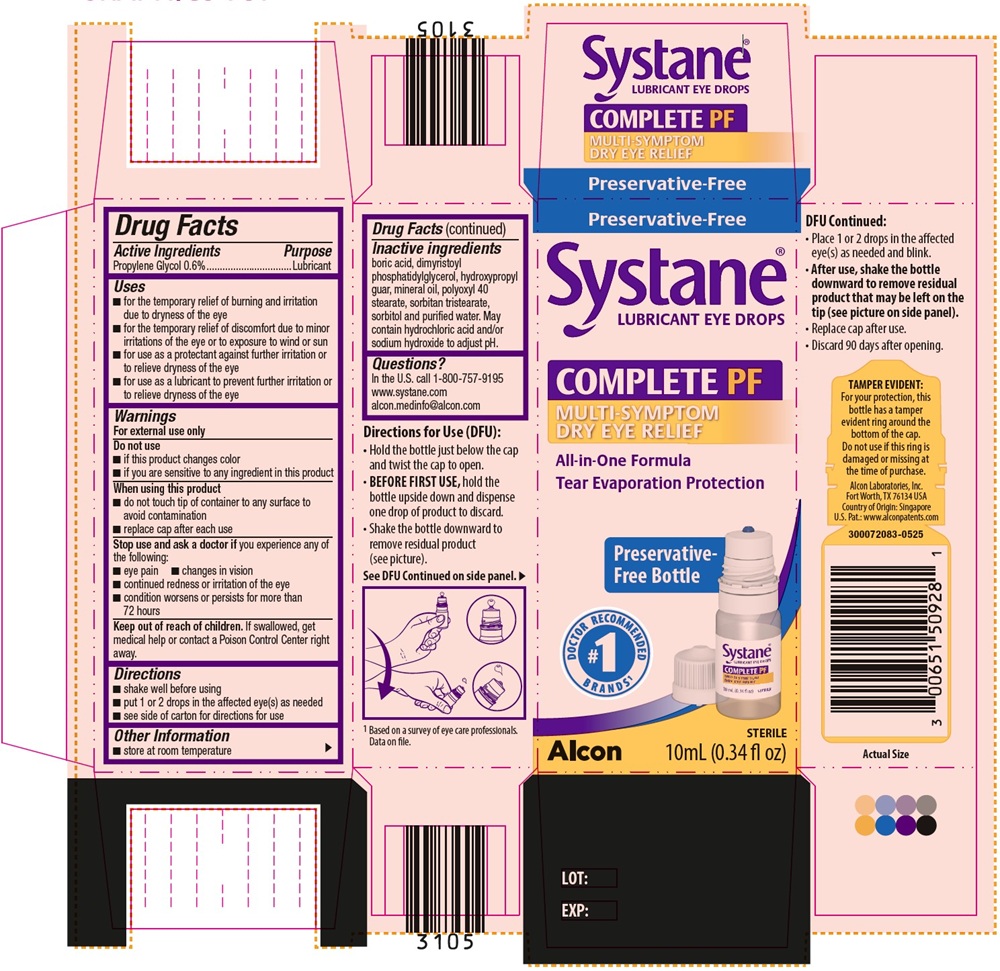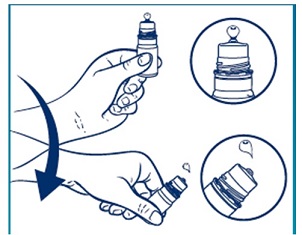 DRUG LABEL: Systane COMPLETE PF
NDC: 0065-1509 | Form: EMULSION
Manufacturer: Alcon Laboratories, Inc.
Category: otc | Type: HUMAN OTC DRUG LABEL
Date: 20250729

ACTIVE INGREDIENTS: Propylene Glycol .06 mg/1 mL
INACTIVE INGREDIENTS: Boric Acid; Dimyristoylphosphatidylglycerol, Dl-; Guaraprolose (3500 Mpa.S At 1%); Mineral Oil; Polyoxyl 40 Stearate; Sorbitan Tristearate; Sorbitol; Water; Hydrochloric Acid; Sodium Hydroxide

SYSTANE COMPLETE PF PRESERVATIVE FREE- Propylene Glycol Emulsion
Drug Facts

Active Ingredients | Purpose
Propylene Glycol 0.6% | Lubricant

Uses

- for the temporary relief of burning and irritation due to dryness of the eye
- for the temporary relief of discomfort due to minor irritations of the eye or to exposure to wind or sun
- for use as a protectant against further irritation or to relieve dryness of the eye
- for use as a lubricant to prevent further irritation or to relieve dryness of the eye

Warnings

For external use only

Do not use

- if this product changes color
- if you are sensitive to any ingredient in this product

When using this product

- do not touch tip of container to any surface to avoid contamination
- replace cap after each use

Stop use and ask a doctor if you experience any of the following:

- eye pain
- changes in vision
- continued redness or irritation of the eye
- condition worsens or persists for more than 72 hours

Keep out of reach of children.
If swallowed, get medical help or contact a Poison Control Center right away.

Directions

- shake well before using
- put 1 or 2 drops in the affected eye(s) as needed
- see side of carton for directions for use

Other Information

- store at room temperature

Inactive Ingredients

boric acid, dimyristoyl phosphatidylglycerol, hydroxypropyl guar, mineral oil, polyoxyl 40 stearate, sorbitan tristearate, sorbitol and purified water. May contain hydrochloric acid and/or sodium hydroxide to adjust pH.

Questions?

In the U.S. call 1-800-757-9195
www.systane.com
alcon.medinfo@alcon.com

Directions for Use (DFU):

- Hold the bottle just below the cap and twist the cap to open.
- BEFORE FIRST USE, hold the bottle upside down and dispense one drop of product to discard.
- Shake the bottle downward to remove residual product (see picture).

- Place 1 or 2 drops in the affected eye(s) as needed and blink.
- After use, shake the bottle downward to remove residual product that may be left on the tip (see picture on side panel).
- Replace cap after use.
- Discard 90 days after opening.

PRINCIPAL DISPLAY PANEL

Preservative-Free
Systane® LUBRICANT EYE DROPS
COMPLETE PF
MULTI-SYMPTOM
DRY EYE RELIEF
All-in-One Formula
Tear evaporation protection
Preservative-Free Bottle
#1 DOCTOR RECOMMENDED BRANDS^1
Alcon
Sterile
10mL (0.34 FL OZ)
LOT: EXP.:
Side Panel:
TAMPER EVIDENT:
For your protection, this bottle has a tamper evident ring around the bottom of the cap. Do not use if this ring is damaged or missing at the time of purchase.
^1Based on a survey of eye care professionals. Data on file.
Alcon Laboratories, Inc.
Fort Worth, TX 76134 USA
Country of Origin United States
U.S. Patent.: www.alconpatents.com
Actual Size
300068244-0824

TWIN VALUE PACK
Preservative-Free
Systane® LUBRICANT EYE DROPS
COMPLETE PF
MULTI-SYMPTOM
DRY EYE RELIEF
All-in-One Formula
Tear evaporation protection
Preservative-Free Bottles
#1 DOCTOR RECOMMENDED BRANDS^1
Alcon
Sterile
Two 10mL (0.34 FL OZ) Bottles
LOT: EXP.:
Side Panel:
TAMPER EVIDENT:
For your protection, this bottle has a tamper evident ring around the bottom of the cap. Do not use if this ring is damaged or missing at the time of purchase.
^1Based on a survey of eye care professionals. Data on file.
Preservative-Free Multi-Symptom Relief for Sensitive Eyes
Alcon Laboratories, Inc.
Fort Worth, TX 76134 USA
Country of Origin United States
U.S. Pat.: www.alconpatents.com
ACTUAL SIZE
300068245-0824

3 PACK
Preservative-Free
Systane® LUBRICANT EYE DROPS
COMPLETE PF
MULTI-SYMPTOM
DRY EYE RELIEF
All-in-One Formula
Tear evaporation protection
Preservative-Free Bottles
#1 DOCTOR RECOMMENDED BRANDS^1
Alcon
Sterile
Three 10mL (0.34 FL OZ) Bottles
LOT: EXP.:
Side Panel:
TAMPER EVIDENT:
For your protection, this bottle has a tamper evident ring around the bottom of the cap. Do not use if this ring is damaged or missing at the time of purchase.
^1Based on a survey of eye care professionals. Data on file.
Preservative-Free Multi-Symptom Relief for Sensitive Eyes
Alcon Laboratories, Inc.
Fort Worth, TX 76134 USA
Country of Origin United States
U.S. Pat.: www.alconpatents.com
ACTUAL SIZE
300068247-0824

Preservative-Free
Systane®
LUBRICANT EYE DROPS
COMPLETE PF
MULTI-SYMPTOM
DRY EYE RELIEF
All-in-One Formula
Tear evaporation protection
Preservative-Free Bottle
#1 DOCTOR RECOMMENDED BRANDS^1
Alcon
Sterile
10mL (0.34 fl oz)
LOT: EXP.:
Side Panel:
TAMPER EVIDENT:
For your protection, this bottle has a tamper evident ring around the bottom of the cap. Do not use if this ring is damaged or missing at the time of purchase.
^1Based on a survey of eye care professionals. Data on file.
Alcon Laboratories, Inc.
Fort Worth, TX 76134 USA
Country of Origin: Singapore
U.S. Pat.: www.alconpatents.com
Actual Size
300072083-0525